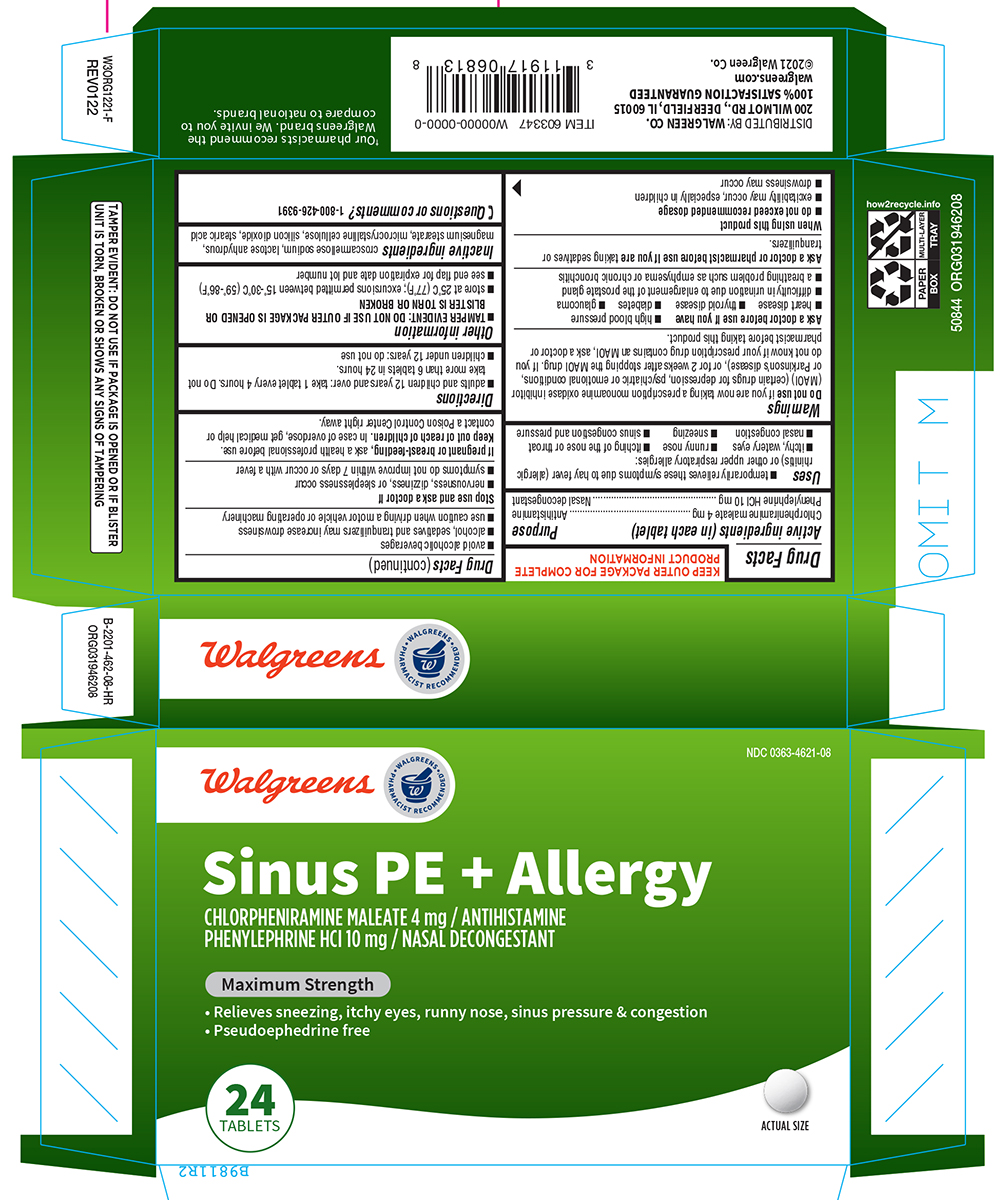 DRUG LABEL: Sinus PE plus Allergy
NDC: 0363-4621 | Form: TABLET
Manufacturer: Walgreen Company
Category: otc | Type: HUMAN OTC DRUG LABEL
Date: 20260113

ACTIVE INGREDIENTS: CHLORPHENIRAMINE MALEATE 4 mg/1 1; PHENYLEPHRINE HYDROCHLORIDE 10 mg/1 1
INACTIVE INGREDIENTS: CROSCARMELLOSE SODIUM; ANHYDROUS LACTOSE; MAGNESIUM STEARATE; MICROCRYSTALLINE CELLULOSE; SILICON DIOXIDE; STEARIC ACID

Walgreens 44-462- Sinus PE Allergy

Active ingredients (in each tablet)

Chlorpheniramine maleate 4 mg
Phenylephrine HCl 10 mg

Purpose

Antihistamine
Nasal decongestant

Uses

- temporarily relieves these symptoms due to hay fever (allergic rhinitis) or other upper respiratory allergies:
  - runny nose
  - sneezing
  - itching of the nose or throat
  - itchy, watery eyes
  - sinus congestion and pressure
  - nasal congestion

Warnings

Do not use

if you are now taking a prescription monoamine oxidase inhibitor (MAOI) (certain drugs for depression, psychiatric or emotional conditions, or Parkinson’s disease), or for 2 weeks after stopping the MAOI drug. If you do not know if your prescription drug contains an MAOI, ask a doctor or pharmacist before taking this product.

Ask a doctor before use if you have

- high blood pressure
- heart disease
- thyroid disease
- diabetes
- glaucoma
- a breathing problem such as emphysema or chronic bronchitis
- difficulty in urination due to enlargement of the prostate gland

Ask a doctor or pharmacist before use if you are

taking sedatives or tranquilizers.

When using this product

- do not exceed recommended dosage
- excitability may occur, especially in children
- drowsiness may occur
- avoid alcoholic beverages
- alcohol, sedatives and tranquilizers may increase drowsiness
- use caution when driving a motor vehicle or operating machinery

Stop use and ask a doctor if

- nervousness, dizziness, or sleeplessness occur
- symptoms do not improve within 7 days or occur with a fever

If pregnant or breast-feeding,

ask a health professional before use.

Keep out of reach of children.

In case of overdose, get medical help or contact a Poison Control Center right away.

Directions

- adults and children 12 years and over: take 1 tablet every 4 hours. Do not take more than 6 tablets in 24 hours.
- children under 12 years: do not use

Other information

- TAMPER EVIDENT: DO NOT USE IF OUTER PACKAGE IS OPENED OR BLISTER IS TORN OR BROKEN
- store at 25°C (77°F); excursions permitted between 15°-30°C (59°-86°F)
- see end flap for expiration date and lot number

Inactive ingredients

croscarmellose sodium, lactose anhydrous, magnesium stearate, microcrystalline cellulose, silicon dioxide, stearic acid

Questions or comments?

1-800-426-9391

Principal display panel

Walgreens

• WALGREENS •
PHARMACIST RECOMMENDED†

NDC 0363-4621-08

Sinus PE + Allergy

CHLORPHENIRAMINE MALEATE 4 mg / ANTIHISTAMINE
PHENYLEPHRINE HCl 10 mg / NASAL DECONGESTANT

Maximum Strength

• Relieves sneezing, itchy eyes, runny nose, sinus pressure & congestion
• Pseudoephedrine free

24
TABLETS

ACTUAL SIZE

TAMPER EVIDENT: DO NOT USE IF PACKAGE IS OPENED OR IF BLISTER
UNIT IS TORN, BROKEN OR SHOWS ANY SIGNS OF TAMPERING

50844 ORG031946208

†Our Pharmacists recommend the
Walgreens Brand. We invite you to
compare to national brands.

DISTRIBUTED BY: WALGREEN CO.
200 WILMOT RD., DEERFIELD, IL 60015
100% SATISFACTION GUARANTEED
walgreens.com
©2021 Walgreen Co.

Walgreens 44-462